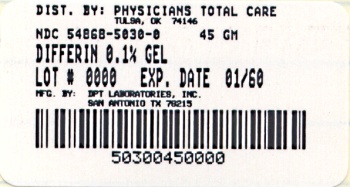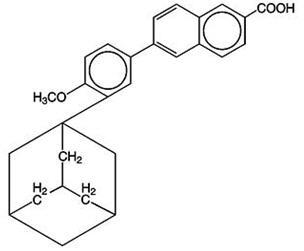 DRUG LABEL: DIFFERIN 
NDC: 54868-5030 | Form: GEL
Manufacturer: Physicians Total Care, Inc.
Category: prescription | Type: HUMAN PRESCRIPTION DRUG LABEL
Date: 20120307

ACTIVE INGREDIENTS: adapalene 1 mg/1 g
INACTIVE INGREDIENTS: Carbomer Homopolymer Type C; Edetate disodium; Methylparaben; Poloxamer 182; Propylene Glycol; Water; Sodium hydroxide; Hydrochloric acid

DIFFERIN®
(adapalene gel)
Gel, 0.1%
Rx Only

DESCRIPTION

DIFFERIN® Gel, containing adapalene, is used for the topical treatment of acne vulgaris. Each gram of DIFFERIN Gel contains adapalene 0.1% (1 mg) in a vehicle consisting of carbomer 940, edetate disodium, methylparaben, poloxamer 182, propylene glycol, purified water and sodium hydroxide. May contain hydrochloric acid to adjust pH.

The chemical name of adapalene is 6-[3-(1-adamantyl)-4-methoxyphenyl]-2-naphthoic acid. Adapalene is a white to off-white powder which is soluble in tetrahydrofuran, sparingly soluble in ethanol, and practically insoluble in water. The molecular formula is C28H28O3 and molecular weight is 412.52. Adapalene is represented by the following structural formula:

CLINICAL PHARMACOLOGY

Adapalene is a chemically stable, retinoid-like compound. Biochemical and pharmacological profile studies have demonstrated that adapalene is a modulator of cellular differentiation, keratinization, and inflammatory processes all of which represent important features in the pathology of acne vulgaris.

Mechanistically, adapalene binds to specific retinoic acid nuclear receptors but does not bind to the cytosolic receptor protein. Although the exact mode of action of adapalene is unknown, it is suggested that topical adapalene may normalize the differentiation of follicular epithelial cells resulting in decreased microcomedone formation.

Pharmacokinetics:

Absorption of adapalene through human skin is low. Only trace amounts (<0.25 ng/mL) of parent substance have been found in the plasma of acne patients following chronic topical application of adapalene in controlled clinical trials. Excretion appears to be primarily by the biliary route.

INDICATIONS AND USAGE

DIFFERIN Gel is indicated for the topical treatment of acne vulgaris.

CONTRAINDICATIONS

DIFFERIN Gel should not be administered to individuals who are hypersensitive to adapalene or any of the components in the vehicle gel.

WARNINGS

Use of DIFFERIN Gel should be discontinued if hypersensitivity to any of the ingredients is noted. Patients with sunburn should be advised not to use the product until fully recovered.

PRECAUTIONS

General:

If a reaction suggesting sensitivity or chemical irritation occurs, use of the medication should be discontinued. Exposure to sunlight, including sunlamps, should be minimized during the use of adapalene. Patients who normally experience high levels of sun exposure, and those with inherent sensitivity to sun, should be warned to exercise caution. Use of sunscreen products and protective clothing over treated areas is recommended when exposure cannot be avoided. Weather extremes, such as wind or cold, also may be irritating to patients under treatment with adapalene.

Avoid contact with the eyes, lips, angles of the nose, and mucous membranes. The product should not be applied to cuts, abrasions, eczematous skin, or sunburned skin.

Certain cutaneous signs and symptoms such as erythema, dryness, scaling, burning, or pruritus may be experienced during treatment. These are most likely to occur during the first two to four weeks and will usually lessen with continued use of the medication. Depending upon the severity of adverse events, patients should be instructed to reduce the frequency of application or discontinue use.

Drug Interactions:

As DIFFERIN Gel has the potential to produce local irritation in some patients, concomitant use of other potentially irritating topical products (medicated or abrasive soaps and cleansers, soaps and cosmetics that have a strong drying effect, and products with high concentrations of alcohol, astringents, spices, or lime) should be approached with caution. Particular caution should be exercised in using preparations containing sulfur, resorcinol, or salicylic acid in combination with DIFFERIN Gel. If these preparations have been used, it is advisable not to start therapy with DIFFERIN Gel until the effects of such preparations in the skin have subsided.

Carcinogenesis, Mutagenesis, Impairment of Fertility:

Carcinogenicity studies with adapalene have been conducted in mice at topical doses of 0.3, 0.9, and 2.6 mg/kg/day and in rats at oral doses of 0.15, 0.5, and 1.5 mg/kg/day, approximately 4-75 times the maximal daily human topical dose. In the oral study, positive linear trends were observed in the incidence of follicular cell adenomas and carcinomas in the thyroid glands of female rats, and in the incidence of benign and malignant pheochromocytomas in the adrenal medullas of male rats.

No photocarcinogenicity studies were conducted. Animal studies have shown an increased tumorigenic risk with the use of pharmacologically similar drugs (e.g., retinoids) when exposed to UV irradiation in the laboratory or to sunlight. Although the significance of these studies to human use is not clear, patients should be advised to avoid or minimize exposure to either sunlight or artificial UV irradiation sources.

In a series of in vivo and in vitro studies, adapalene did not exhibit mutagenic or genotoxic activities.

Pregnancy:

TERATOGENIC EFFECTS

Teratogenic Effects. Pregnancy Category C. No teratogenic effects were seen in rats at oral doses of adapalene 0.15 to 5.0 mg/kg/day, up to 120 times the maximal daily human topical dose. Cutaneous route teratology studies conducted in rats and rabbits at doses of 0.6, 2.0, and 6.0 mg/kg/day, up to 150 times the maximal daily human topical dose exhibited no fetotoxicity and only minimal increases in supernumerary ribs in rats. There are no adequate and well-controlled studies in pregnant women. Adapalene should be used during pregnancy only if the potential benefit justifies the potential risk to the fetus.

Nursing Mothers:

It is not known whether this drug is excreted in human milk. Because many drugs are excreted in human milk, caution should be exercised when DIFFERIN Gel is administered to a nursing woman.

Pediatric Use:

Safety and effectiveness in pediatric patients below the age of 12 have not been established.

ADVERSE REACTIONS

Some adverse effects such as erythema, scaling, dryness, pruritus, and burning will occur in 10-40% of patients. Pruritus or burning immediately after application also occurs in approximately 20% of patients. The following additional adverse experiences were reported in approximately 1% or less of patients: skin irritation, burning/stinging, erythema, sunburn, and acne flares. These are most commonly seen during the first month of therapy and decrease in frequency and severity thereafter. All adverse effects with use of DIFFERIN Gel during clinical trials were reversible upon discontinuation of therapy.

OVERDOSAGE

DIFFERIN Gel is intended for cutaneous use only. If the medication is applied excessively, no more rapid or better results will be obtained and marked redness, peeling, or discomfort may occur. The acute oral toxicity of DIFFERIN Gel in mice and rats is greater than 10 mL/kg. Chronic ingestion of the drug may lead to the same side effects as those associated with excessive oral intake of Vitamin A.

DOSAGE AND ADMINISTRATION

DIFFERIN Gel should be applied once a day to affected areas after washing in the evening before retiring. A thin film of the gel should be applied, avoiding eyes, lips, and mucous membranes.

During the early weeks of therapy, an apparent exacerbation of acne may occur. This is due to the action of the medication on previously unseen lesions and should not be considered a reason to discontinue therapy. Therapeutic results should be noticed after eight to twelve weeks of treatment.

HOW SUPPLIED

DIFFERIN (adapalene gel) Gel, 0.1% is supplied in the following size:

45 g laminate tube - NDC 54868-5030-0

Storage:

Store at controlled room temperature 20° - 25°C (68° - 77°F).

Marketed by:
GALDERMA LABORATORIES, L.P.
Fort Worth, Texas 76177 USA
Mfd. by:
DPT Laboratories, Ltd.
San Antonio, TX 78215
Mfd. by:
Galderma Production Canada, Inc.
Baie d’Urfe, QC, H9X 3S4 Canada
Made in Canada.
GALDERMA is a registered trademark.
325034-0903
P50045-0
Revised: September 2003

Additional barcode labeling by:
Physicians Total Care, Inc.
Tulsa, Oklahoma 74146

PACKAGE LABEL

Differin®
(adapalene gel)

GEL

0.1%

NET WT. 45 g

NDC 54868-5030-0

Rx Only

For External Use Only. Not For Ophthalmic Use. Store at controlled room temperature 68° to 77°F (20°-25°C).

Usual dosage: Apply a thin film once a day to affected areas after washing in the evening before retiring. See package insert for complete prescribing information.

Each gram contains: adapalene 0.1% (1 mg) in a vehicle consisting of carbomer 940, edetate disodium, methylparaben, poloxamer 182, propylene glycol, purified water, and sodium hydroxide. May contain hydrochloric acid to adjust pH.